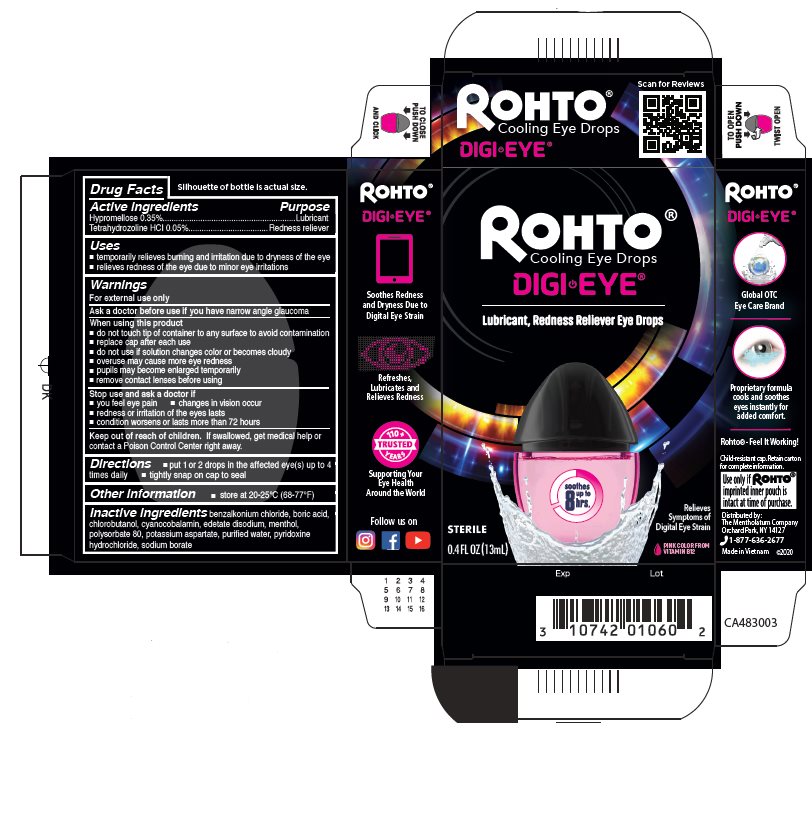 DRUG LABEL: Rohto Digi-Eye
NDC: 10742-8175 | Form: LIQUID
Manufacturer: The Mentholatum Company
Category: otc | Type: HUMAN OTC DRUG LABEL
Date: 20241217

ACTIVE INGREDIENTS: HYPROMELLOSE, UNSPECIFIED 3.5 mg/1 mL; TETRAHYDROZOLINE HYDROCHLORIDE 0.5 mg/1 mL
INACTIVE INGREDIENTS: BENZALKONIUM CHLORIDE; BORIC ACID; CHLOROBUTANOL; CYANOCOBALAMIN; EDETATE DISODIUM; MENTHOL, UNSPECIFIED FORM; POLYSORBATE 80; POTASSIUM ASPARTATE; WATER; PYRIDOXINE HYDROCHLORIDE; SODIUM BORATE

Drug Facts - Rohto Digi-Eye

Active ingredients

Hypromellose 0.35%

Tetrahydrozoline hydrochloride 0.05%

Purpose

Hypromellose - Lubricant

Tetrahydrozoline hydrochloride - Redness reliever

Uses

- temporarily relieves burning and irritation due to dryness of the eye
- relieves redness of the eye due to minor eye irritations

Warnings

For external use only

Ask a doctor before use if you have

narrow angle glaucoma

When using this product

- do not touch tip of container to any surface to avoid contamination
- replace cap after each use
- do not use if solution changes color or becomes cloudy
- overuse may cause more eye redness
- pupils may become enlarged temporarily
- remove contact lenses before using

Stop use and ask a doctor if

- you feel eye pain
- changes in vision occur
- redness or irritation of the eyes lasts
- condition worsens or lasts more than 72 hours

Keep out of reach of children.

If swallowed, get medical help or contact a Poison Control Center right away.

Directions

- put 1 or 2 drops in the affected eye(s) up to 4 times daily
- tightly snap on cap to seal

Other information

- store at 20-25°C (68-77°F)

Inactive ingredients

benzalkonium chloride, boric acid, chlorobutanol, cyanocobalamin, edetate disodium, menthol, polysorbate 80, potassium aspartate, purified water, pyridoxine hydrochloride, sodium borate

Questions or comments?

1-877-636-2677 MON-FRI 9AM to 5PM (EST)